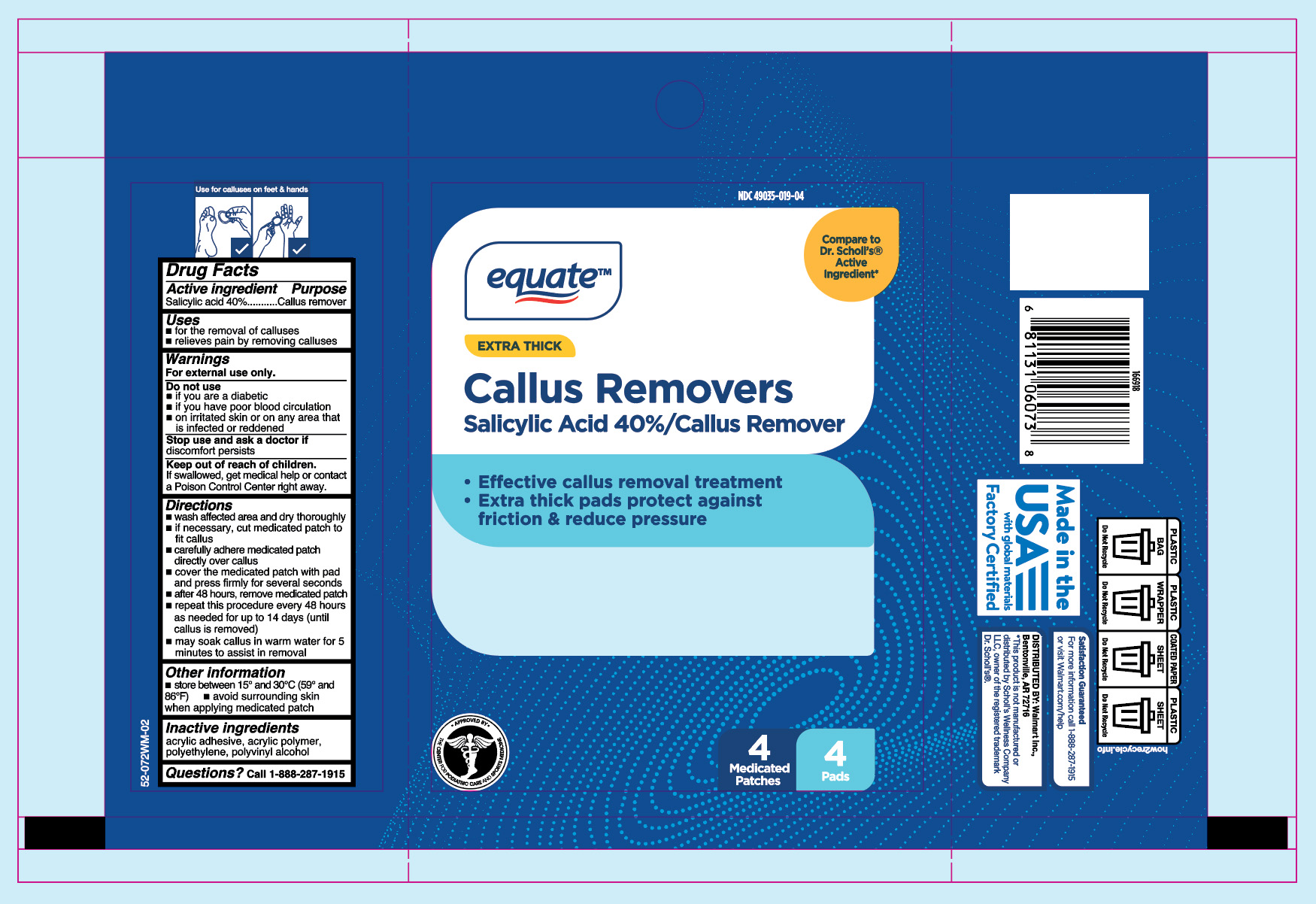 DRUG LABEL: Extra Thick Callus Removers
NDC: 49035-019 | Form: PATCH
Manufacturer: Wal-Mart Stores, Inc.
Category: otc | Type: HUMAN OTC DRUG LABEL
Date: 20260130

ACTIVE INGREDIENTS: SALICYLIC ACID 40 mg/100 mg
INACTIVE INGREDIENTS: POLYVINYL ALCOHOL; HIGH DENSITY POLYETHYLENE

Equate Extra Thick Callus Removers

Active ingredient

Salicylic acid 40%

Purpose

Callus remover

Uses

- for the removal of calluses
- relieves pain by removing calluses

Warnings

For external use only.

Do not use

- if you are diabetic
- if you have poor blood circulation
- on irritated skin or any area that is infected or reddened

Stop use and ask a doctor if

discomfort persists

Keep out of reach of children.

If swallowed, get medical help or contact a Poison Control Center right away.

Directions

- wash affected area and dry thoroughly
- if necessary, cut medicated patch to fit callus
- carefully adhere medicated patch directly over callus
- cover the medicated patch with pad and press firmly for several seconds
- after 48 hours, remove medicated patch
- repeat this procedure every 48 hours as needed for up to 14 days (until callus is removed)
- may soak callus in warm water for 5 minutes to assist in removal

Other information

- store between 15° and 30°C (59° and 86°F)
- avoid surrounding skin when applying medicated patch

Inactive ingredients

acrylic adhesive, acrylic polymer, polyethylene, polyvinyl alcohol

Questions?

call 1-888-287-1915

Principal Display Panel

Equate

EXTRA THICK

Callus Removers

Salicylic Acid 40% / Callus Remover

- Effective callus removal treatment
- Extra thick pads protect against

friction & reduce pressure

4 Medicated Patches/ 4 Pads